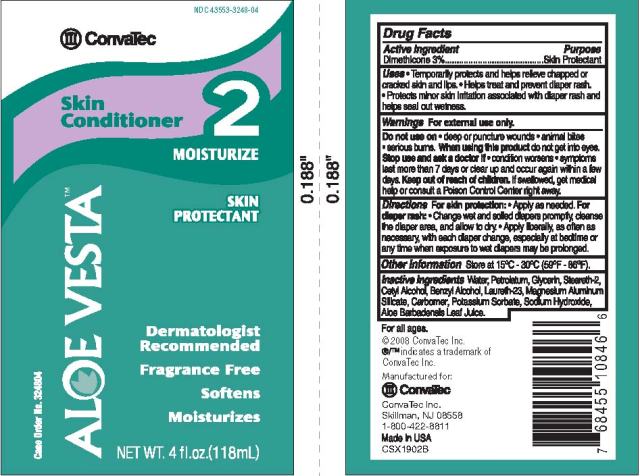 DRUG LABEL: ALOE VESTA SKIN CONDITIONER
NDC: 43553-3248 | Form: LOTION
Manufacturer: ConvaTec, Inc.
Category: otc | Type: HUMAN OTC DRUG LABEL
Date: 20110414

ACTIVE INGREDIENTS: DIMETHICONE .03 mg/1 mL
INACTIVE INGREDIENTS: WATER; PETROLATUM; GLYCERIN; STEARETH-2; CETYL ALCOHOL; BENZYL ALCOHOL; LAURETH-23; MAGNESIUM ALUMINUM SILICATE; CARBOMER 934; POTASSIUM SORBATE; SODIUM HYDROXIDE; ALOE VERA LEAF

Drug Facts

Active Ingredient

Dimethicone 3%

Purpose

Skin Protectant

Uses

- Temporarily protects and helps relieve chapped or cracked skin and lips.
- Helps treat and prevent diaper rash.
- Protects minor skin irritation associated with diaper rash and helps seal out wetness.

Warnings

For external use only.

Do not use on

- deep or puncture wounds
- animal bites
- serious burns

When using this product

do not get into eyes.

Stop use and ask a doctor if

- condition worsens
- symptoms last more than 7 days or clear up and occur again within a few days.

Keep out of reach of children.

If swallowed, get medical help or consult a Poison Control Center right away.

Directions

For skin protection:

- Apply as needed.

For diaper rash:

- Change wet and soiled diapers promptly, cleanse the diaper area, and allow to dry.
- Apply liberally, as often as necessary, with each diaper change, especially at bedtime or any time when exposure to wet diapers may be prolonged.

Other Information

Store at 15oC - 30oC (59oF - 86oF).

Inactive Ingredients

Water, Petrolatum, Glycerin, Steareth-2, Cetyl Alcohol, Benzyl Alcohol, Laureth-23, Magnesium Aluminum Silicate, Carbomer, Potassium Sorbate, Sodium Hydroxide, Aloe Barbadensis Leaf Juice.

PRINCIPAL DISPLAY PANEL

NDC 43553-3248-4
ConvaTec

ALOE VESTATM

Skin Conditioner 2
MOISTURIZE
SKIN PROTECTANT
Dermatologist Recommended
Fragrance Free

Softens

Moisturizes
NET WT. 4 fl.oz.(118mL)

Case Order No. 324804